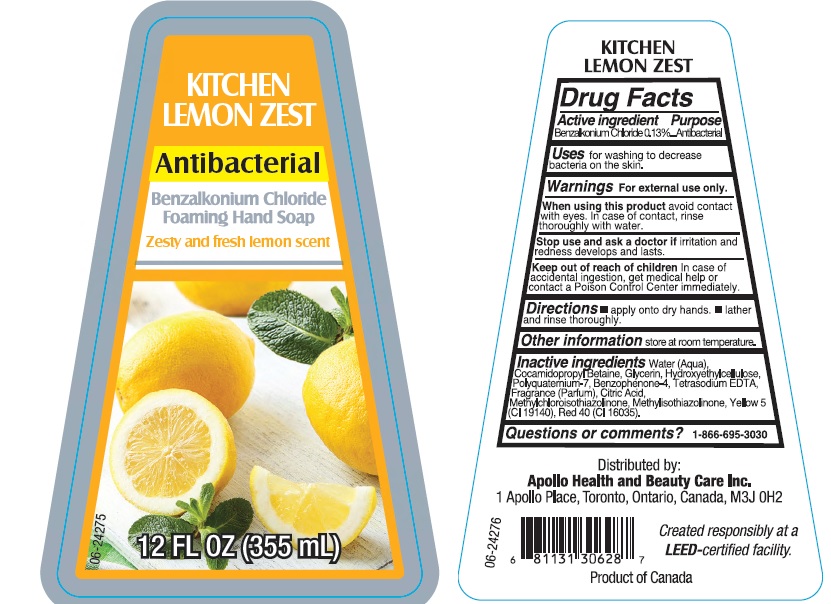 DRUG LABEL: Kitchen Lemon Zest Antibacterial Foaming Hand
NDC: 63148-016 | Form: SOAP
Manufacturer: Apollo Health and Beauty Care Inc.
Category: otc | Type: HUMAN OTC DRUG LABEL
Date: 20190821

ACTIVE INGREDIENTS: BENZALKONIUM CHLORIDE 1.3 mg/1 mL
INACTIVE INGREDIENTS: WATER; COCAMIDOPROPYL BETAINE; GLYCERIN; HYDROXYETHYL CELLULOSE (5000 CPS AT 1%); POLYQUATERNIUM-7 (70/30 ACRYLAMIDE/DADMAC; 1600000 MW); SULISOBENZONE; EDETATE SODIUM; CITRIC ACID MONOHYDRATE; METHYLCHLOROISOTHIAZOLINONE; METHYLISOTHIAZOLINONE; FD&C YELLOW NO. 5; FD&C RED NO. 40

Drug Facts

Active ingredient

Benzalkonium Chloride 0.13%

Purpose

Antibacterial

Uses

for washing to decrease bacteria on the skin.

Warnings

For external use only.

When using this product

avoid contact with eyes. In case of contact, rinse thoroughly with water.

Stop use and ask a doctor if

irritation ad redness develops and lasts.

Keep out of reach of children.

In case of accidental ingestiong, get medical help or contact a Poison Control Center immediately.

Directions

- apply onto dry hands
- lather and rinse thoroughly

Other information

store at room temperature

Inactive ingredients

Water (Aqua), Cocamidopropyl Betaine, Glycerin, Hydroxyethylcellulose, Polyquaternium-7, Benzophenone-4, Tetrasodium EDTA, Fragrance (Parfum), Citric Acid, Methylchloroisothiazolinone, Methylisothiazolinone, Yellow 5 (CI 19140), Red 40 (CI 16035).

Questions or comments?

1-866-695-3030